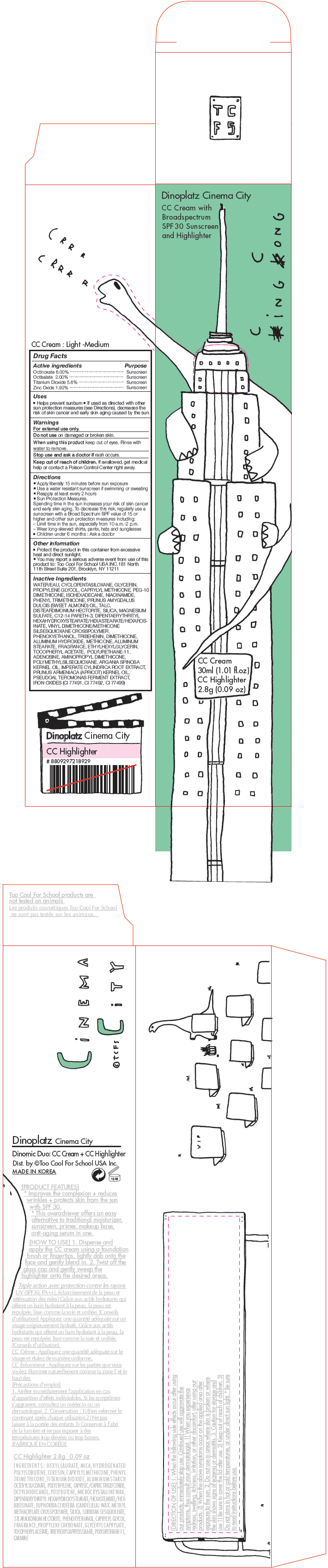 DRUG LABEL: Too Cool For School
NDC: 69926-001 | Form: KIT | Route: TOPICAL
Manufacturer: Too Cool For School USA, Inc
Category: otc | Type: HUMAN OTC DRUG LABEL
Date: 20150630

ACTIVE INGREDIENTS: Octinoxate 60 mg/1 mL; Octisalate 20 mg/1 mL; Titanium Dioxide 56 mg/1 mL; Zinc Oxide 19.2 mg/1 mL
INACTIVE INGREDIENTS: WATER; CYCLOMETHICONE 5; GLYCERIN; PROPYLENE GLYCOL; CAPRYLYL TRISILOXANE; ISOHEXADECANE; NIACINAMIDE; PHENYL TRIMETHICONE; ALMOND OIL; TALC; DISTEARDIMONIUM HECTORITE; SILICON DIOXIDE; MAGNESIUM SULFATE; C12-14 PARETH-3; PHENOXYETHANOL; TRIBEHENIN; DIMETHICONE; ALUMINUM HYDROXIDE; ALUMINUM STEARATE; ETHYLHEXYLGLYCERIN; .ALPHA.-TOCOPHEROL ACETATE; ADENOSINE; ARGAN OIL; IMPERATA CYLINDRICA ROOT; APRICOT KERNEL OIL; FERRIC OXIDE RED

Too Cool For School

Drug Facts

ACTIVE INGREDIENT

Active ingredients | Purpose
Octinoxate 6.00% | Sunscreen
Octisalate 2.00% | Sunscreen
Titanium Dioxide 5.6% | Sunscreen
Zinc Oxide 1.92% | Sunscreen

Uses

- Helps prevent sunburn
- If used as directed with other sun protection measures (see Directions), decreases the risk of skin cancer and early skin aging caused by the sun.

Warnings

For external use only.

Do not use on damaged or broken skin.

When using this product keep out of eyes. Rinse with water to remove.

Stop use and ask a doctor if rash occurs.

Keep out of reach of children. If swallowed, get medical help or contact a Poison Control Center right away.

Directions

- Apply liberally 15 minutes before sun exposure
- Use a water resistant sunscreen if swimming or sweating
- Reapply at least every 2 hours
- Sun Protection Measures.
  Spending time in the sun increases your risk of skin cancer and early skin aging. To decrease this risk, regularly use a sunscreen with a Broad Spectrum SPF value of 15 or higher and other sun protection measures including:
  – Limit time in the sun, especially from 10 a.m.-2 p.m.
  – Wear long-sleeved shirts, pants, hats and sunglasses
- Children under 6 months : Ask a doctor

Other information

- Protect the product in this container from excessive heat and direct sunlight.
- You may report a serious adverse event from use of this product to: Too Cool For School USA INC.181 North 11th Street Suite 201, Brooklyn, NY 11211

Inactive Ingredients

WATER/EAU, CYCLOPENTASILOXANE, GLYCERIN, PROPYLENE GLYCOL, CAPRYLYL METHICONE, PEG-10 DIMETHICONE, ISOHEXADECANE, NIACINAMIDE, PHENYL TRIMETHICONE, PRUNUS AMYGDALUS DULCIS (SWEET ALMOND) OIL, TALC, DISTEARDIMONIUM HECTORITE, SILICA, MAGNESIUM SULFATE, C12-14 PARETH-3, DIPENTAERYTHRITYL HEXAHYDROXYSTEARATE/HEXASTEARATE/HEXAROSINATE, VINYL DIMETHICONE/METHICONE SILSESQUIOXANE CROSSPOLYMER, PHENOXYETHANOL, TRIBEHENIN, DIMETHICONE, ALUMINUM HYDROXIDE, METHICONE, ALUMINUM STEARATE, FRAGRANCE, ETHYLHEXYLGLYCERIN, TOCOPHERYL ACETATE, POLYURETHANE-11, ADENOSINE, AMINOPROPYL DIMETHICONE, POLYMETHYLSILSEQUIOXANE, ARGANIA SPINOSA KERNEL OIL, IMPERATE CYLINDRICA ROOT EXTRACT, PRUNUS ARMENIACA (APRICOT) KERNEL OIL, PSEUDOAL TEROMONAS FERMENT EXTRACT, IRON OXIDES (CI 77491, CI 77492, CI 77499)

Dist. by ©Too Cool For School USA Inc.

PRINCIPAL DISPLAY PANEL - Kit Carton

Dinoplatz Cinema City

CC Cream with
Broadspectrum
SPF 30 Sunscreen
and Highlighter

cing cong

CC Cream
30ml (1.01 fl.oz)
CC Highlighter
2.8g (0.09 oz)